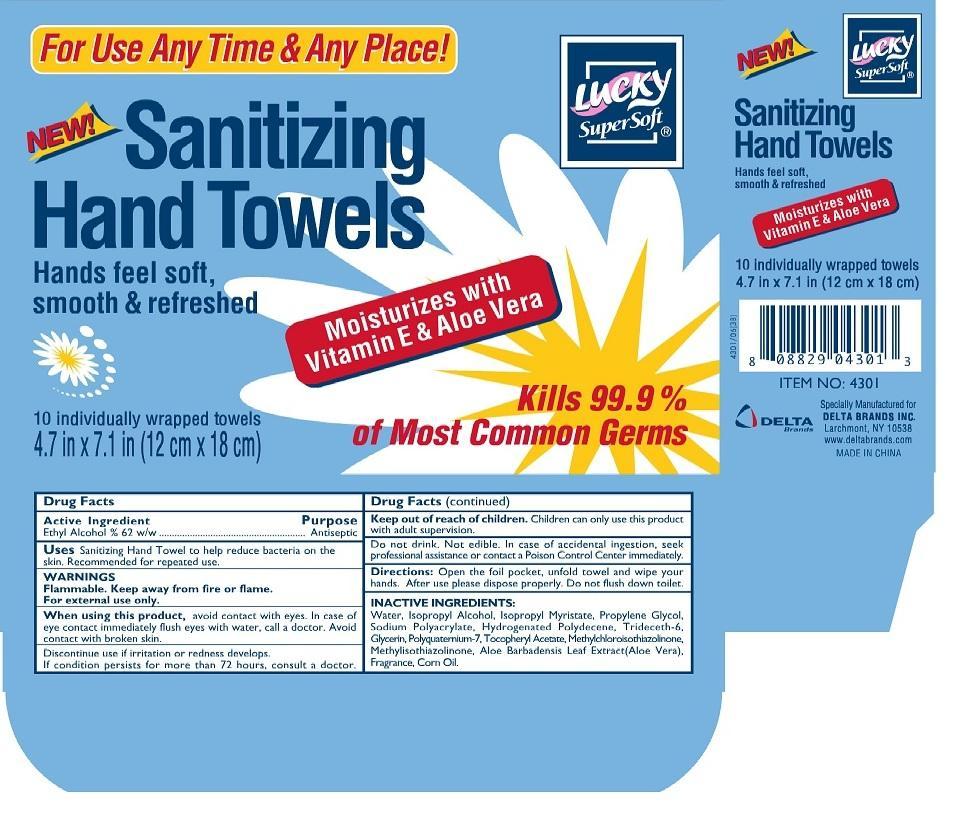 DRUG LABEL: Lucky
NDC: 20276-430 | Form: CLOTH
Manufacturer: Delta Brands, Inc
Category: otc | Type: HUMAN OTC DRUG LABEL
Date: 20130808

ACTIVE INGREDIENTS: ALCOHOL 62 mg/1 1
INACTIVE INGREDIENTS: WATER; ISOPROPYL ALCOHOL; ISOPROPYL MYRISTATE; PROPYLENE GLYCOL; SODIUM POLYACRYLATE (8000 MW); HYDROGENATED POLYDECENE (550 MW); TRIDECETH-6; GLYCERIN; .ALPHA.-TOCOPHEROL ACETATE; METHYLCHLOROISOTHIAZOLINONE; METHYLISOTHIAZOLINONE; ALOE VERA LEAF; CORN OIL

Drug Facts

Active Ingredient

Ethyl alcohol 62%

Purpose

Antiseptic

Uses

Sanitizing Hand Towel to help bacteria on the skin. Recommended for repeated use

WARNINGS

Flammable. Keep away from fire or flame.

For external use only

When using this product

avoid contact with eyes. In case of eye contact immediately flush eyes with water, call a doctor.
Avoid contact with broken skin.

Discontinue use

if irritation or redness develops. If condition persists for more than 72 hours, consult a doctor

Keep out of reach of children

Children can only use this product with adult supervision. Do not drink. Not edible, in case of accidental ingestion seek professional assistance or contact a Poison Control Center immediately

Directions

Open the foil packet, unfold towel and wipe your hands. After use dispose properly. Do not flush down toilet

INACTIVE INGREDIENTS

Water, Isopropyl Alcohol, Isopropyl Myristate, Propylene Glycol, Sodium Polyacrylate, Hydrogenated Polydecene, Trideceth-6, Fragrance, Glycerin, Polyquaternium-7, Tocopheryl Acetate, Methylchloroisothiazolinine, Methylisothiazolinone, Aloe Barbadensis Leaf Extract (Aloe Vera), Fragrance, Corn Oil